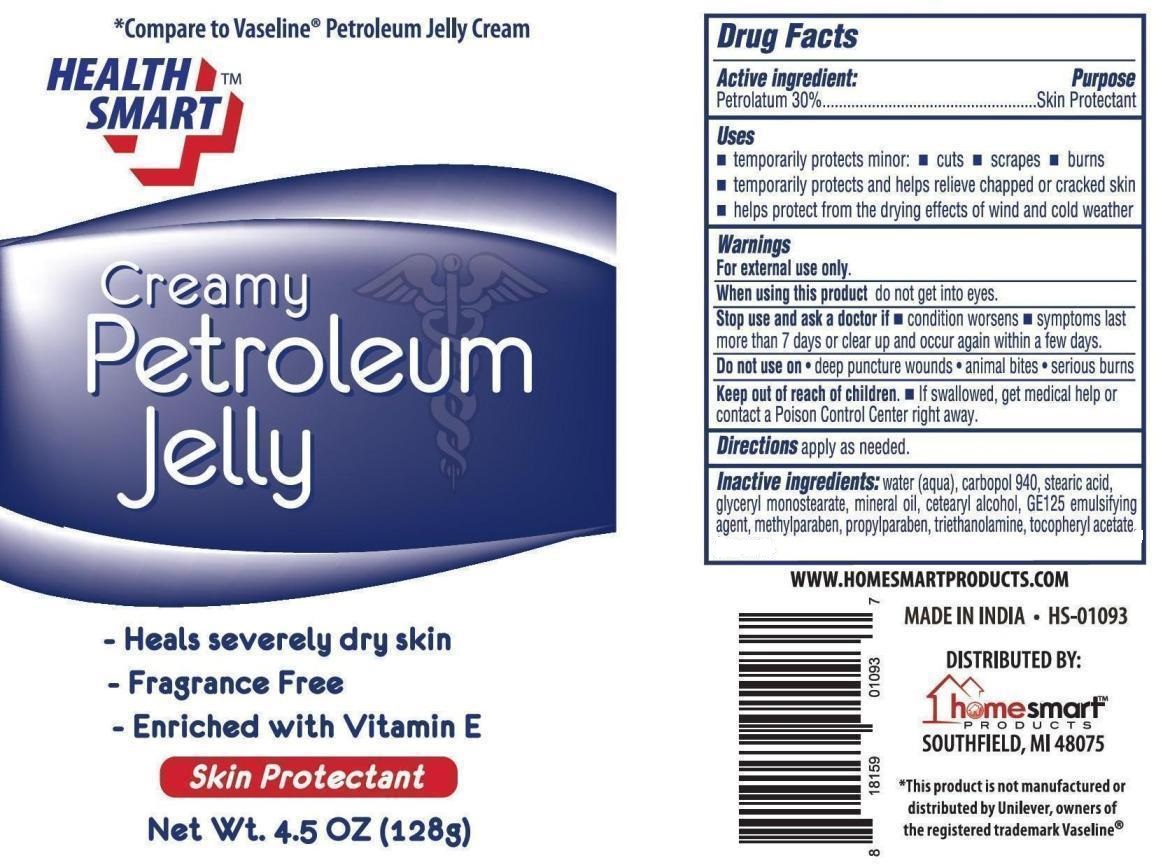 DRUG LABEL: Health Smart Creamy Petroleum
NDC: 52862-018 | Form: JELLY
Manufacturer: International Wholesale Inc dba Home Smart Products
Category: otc | Type: HUMAN OTC DRUG LABEL
Date: 20220131

ACTIVE INGREDIENTS: PETROLATUM 30 g/100 g
INACTIVE INGREDIENTS: WATER; CARBOMER HOMOPOLYMER TYPE C (ALLYL PENTAERYTHRITOL CROSSLINKED); STEARIC ACID; GLYCERYL MONOSTEARATE; MINERAL OIL; CETOSTEARYL ALCOHOL; METHYLPARABEN; PROPYLPARABEN; TROLAMINE; .ALPHA.-TOCOPHEROL ACETATE

Health Smart Creamy Petroleum Jelly

Active Ingredient

Petrolatum 30%

Purpose

Skin Protectant

Uses

- temporarily protects minor; cuts, scrapes or burns.
- temporarily protects and helps relieve chapped or cracked skin.
- helps protect from the drying effects of wind and cold weather.

Warnings

For external use only.

When using this product do not get into eyes.

Stop use and ask a doctor if

- condition worsens
- symptoms last more than 7 days or clear up and occur again within a few days.

Do not use on

- deep puncture wounds
- animal bites
- serious burns

Keep out of reach of children

- if swallowed, get medical help or contact a Poison Control Center right away.

Directions

apply as needed.

Inactive Ingredients

water (aqua), carbopol 940, stearic acid, glyceryl monostearate, mineral oil, cetearyl alcohol, GE125 emulsifying agent, methylparaben, propylparaben, triethanolamine, tocopheryl acetate.

PRINCIPAL DISPLAY PANEL

HEALTH SMART CREAMY PETROLEUM JELLY

NET WT. 4.5 OZ. (128G)